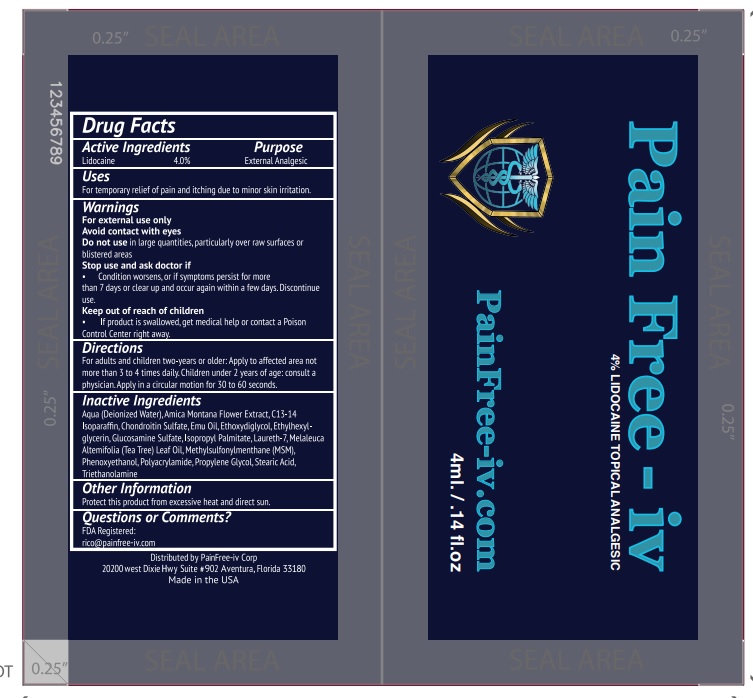 DRUG LABEL: Pain free IV
NDC: 54723-008 | Form: CREAM
Manufacturer: Sambria Pharmaceuticals, LLC
Category: otc | Type: HUMAN OTC DRUG LABEL
Date: 20251007

ACTIVE INGREDIENTS: LIDOCAINE 4 g/100 mL
INACTIVE INGREDIENTS: WATER; ARNICA MONTANA FLOWER; C13-14 ISOPARAFFIN; ELOSULFASE ALFA; EMU OIL; DIETHYLENE GLYCOL MONOETHYL ETHER; ETHYLHEXYLGLYCERIN; GLUCOSAMINE SULFATE; ISOPROPYL PALMITATE; LAURETH-7; TEA TREE OIL; DIMETHYL SULFONE; PHENOXYETHANOL; POLYACRYLAMIDE (10000 MW); PROPYLENE GLYCOL; STEARIC ACID; TROLAMINE

Active ingredient

4% Lidocaine

Purpose

External Anesthetic

Uses

For temporary relief of pain and itching due to minor skin irritations.

Warnings

For external use only.

Avoid contact with eyes.

Do not usein large quantities, particularly over raw surface or blistered areas

Stop use and ask doctor if

Condition worsens or if symptons persists more than 7 days or clear up and occur again within a few days. Discontinue use.

Keep out of reach of children

If swallowed, get medical help or contact a Poison Control Center right away.

Directions

For adults and children two-years or older: Apply to affected area not more than 3 or 4 times daily. Children under 2 years of age: consult a physician.

Inactive ingredients

Aqua (Deionized Water), Arnica Montana Floweri Extract, C13-14 Isoparaffin, Chondroitin Sulfate, Emu Oil, Ethoxydiglycol, Ethylhexylglycerin, Glucosamine Sulfate, Isopropyl Palmitate, Laureth-7, Melaleuca Alternifolia (Tea Tree) Oil, Methylsulfonylmenthane (MSM), Phenoxyethanol, Polyacrylamide, Propylene Glycol, Stearic Acid, Triethanolamine.

Other information

Protect this product from excessive heat and direct sun.

Question or Comments

FDA Registered : rico@painfree-iv.com